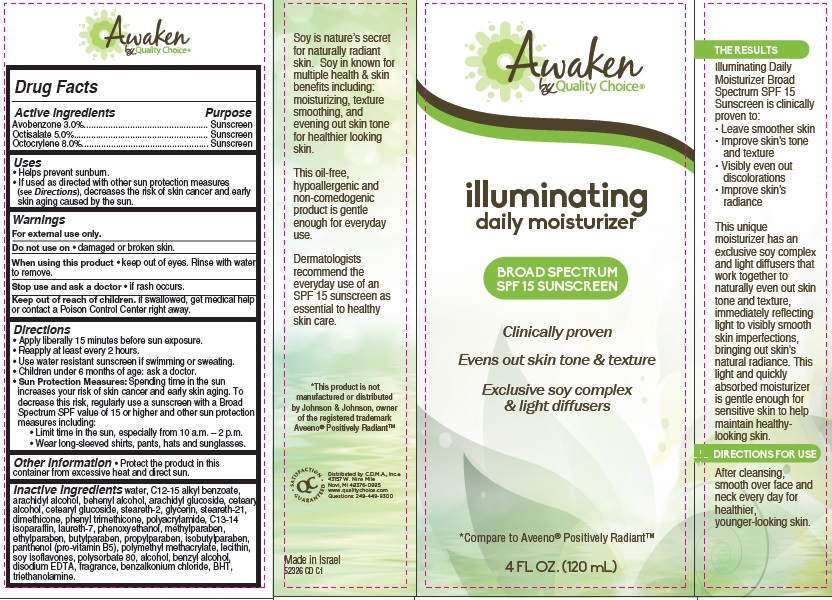 DRUG LABEL: Awaken by Quality Choice Illuminating Daily Moisturizer Broad Spectrum SPF 15 Sunscreen
NDC: 63868-254 | Form: CREAM
Manufacturer: Chain Drug Marketing Association
Category: otc | Type: HUMAN OTC DRUG LABEL
Date: 20141001

ACTIVE INGREDIENTS: AVOBENZONE 3 g/100 g; OCTISALATE 5 g/100 g; OCTOCRYLENE 8 g/100 g
INACTIVE INGREDIENTS: WATER; ALKYL (C12-15) BENZOATE; ARACHIDYL ALCOHOL; DOCOSANOL; ARACHIDYL GLUCOSIDE; CETOSTEARYL ALCOHOL; CETEARYL GLUCOSIDE; STEARETH-2; GLYCERIN; STEARETH-21; DIMETHICONE; PHENYL TRIMETHICONE; C13-14 ISOPARAFFIN; LAURETH-7; PHENOXYETHANOL; METHYLPARABEN; ETHYLPARABEN; BUTYLPARABEN; PROPYLPARABEN; ISOPROPYLPARABEN; PANTHENOL; POLY(METHYL METHACRYLATE; 450000 MW); SOY ISOFLAVONES; POLYSORBATE 80; ALCOHOL; BENZYL ALCOHOL; EDETATE DISODIUM; BENZALKONIUM CHLORIDE; BUTYLATED HYDROXYTOLUENE; TROLAMINE

Awaken by Quality Choice®

Active ingredient

Avobenzone 3.0%

Octisalate 5.0%

Octocrylene 8.0%

Purpose

Sunscreen

Uses

- Helps prevent sunburn.
- If used as directed with other sun protection measures (see Directions), decreases the risk of skin cancer and early skin aging caused by the sun.

Warnings

For external use only.

Do not use on

- damaged or broken skin.

When using this product

- keep out of eyes. Rinse with water to remove.

Stop use and ask a doctor

- if rash occurs.

Keep Out of Reach of Children.

If swallowed, get medical help or contact a Poison Control Center right away.

Directions

- Apply liberally 15 minutes before sun exposure.
- Reapply at least every 2 hours.
- Use water resistant sunscreen if swimming or sweating.
- Children under 6 months of age: ask a doctor.
- Sun Protection Measures: Spending time in the sun increases your risk of skin cancer and early skin aging. To decrease this risk, regularly use a sunscreen with a Broad Spectrum SPF value of 15 or higher and other sun protection measures including:
  1. Limit time in the sun, especially from 10 a.m. – 2 p.m.
  2. Wear long-sleeved shirts, pants, hats and sunglasses.

Other Information

- Protect the product in this container from excessive heat and direct sun.

Inactive ingredients

water, C12-15 alkyl benzoate, arachidyl alcohol, beheynl alcohol, arachidyl glucoside, cetearyl alcohol, cetearyl glucoside, steareth-2, glycerin, steareth-21, dimethicone, phenyl trimethicone, polyacrylamide, C13-14 isoparaffin, laureth-7, phenoxyethanol, methylparaben, ethylparaben, butylparaben, propylparaben, isobutylparaben, panthenol (pro-vitamin B5), polymethyl methacrylate, lecithin, soy isoflavones, polysorbate 80, alcohol, benzyl alcohol, disodium EDTA, fragrance, benzalkonium chloride, BHT, triethanolamine.

Package/Label Principal Display Panel

Awaken
by Quality Choice®

illuminating
daily moisturizer

BROAD SPECTRUM
SPF 15 SUNSCREEN

Clinically proven

Evens out skin tone & texture

Exclusive soy complex
& light diffusers

*Compare to Aveeno® Positively Radiant™

4 FL OZ. (120 mL)

THE RESULTS

Illuminating Daily Moisturizer Broad Spectrum SPF 15 Sunscreen is clinically proven to:

- Leave smoother skin
- Improve skin’s tone and texture
- Visibly even out discolorations
- Improve skin’s radiance

This unique moisturizer has an exclusive soy complex and light diffusers that work together to naturally even out skin tone and texture, immediately reflecting light to visibly smooth skin imperfections, bringing out skin’s natural radiance. This light and quickly absorbed moisturizer is gentle enough for sensitive skin to help maintain healthy-looking skin.

DIRECTIONS FOR USE

After cleansing, smooth over face and neck every day for healthier, younger-looking skin.

Soy is nature’s secret for naturally radiant skin. Soy in known for multiple health & skin benefits including: moisturizing, texture smoothing, and evening out skin tone for healthier looking skin.

This oil-free hypoallergenic and non-comedogenic product is gentle enough for everyday use.

Dermatologists recommend the everyday use of an SPF 15 sunscreen as essential to healthy skin care.

*This product is not manufactured or distributed by Johnson & Johnson, owner of the registered trademark Aveeno® Positively Radiant™

SATISFACTION GUARANTEED

Distributed by C.D.M.A., Inc.©
43157 W. Nine Mile
Novi, MI 48376-0995
www.qualitychoice.com
Questions: 248-449-9300

Made in Israel
52326 CD C1

Carton Label